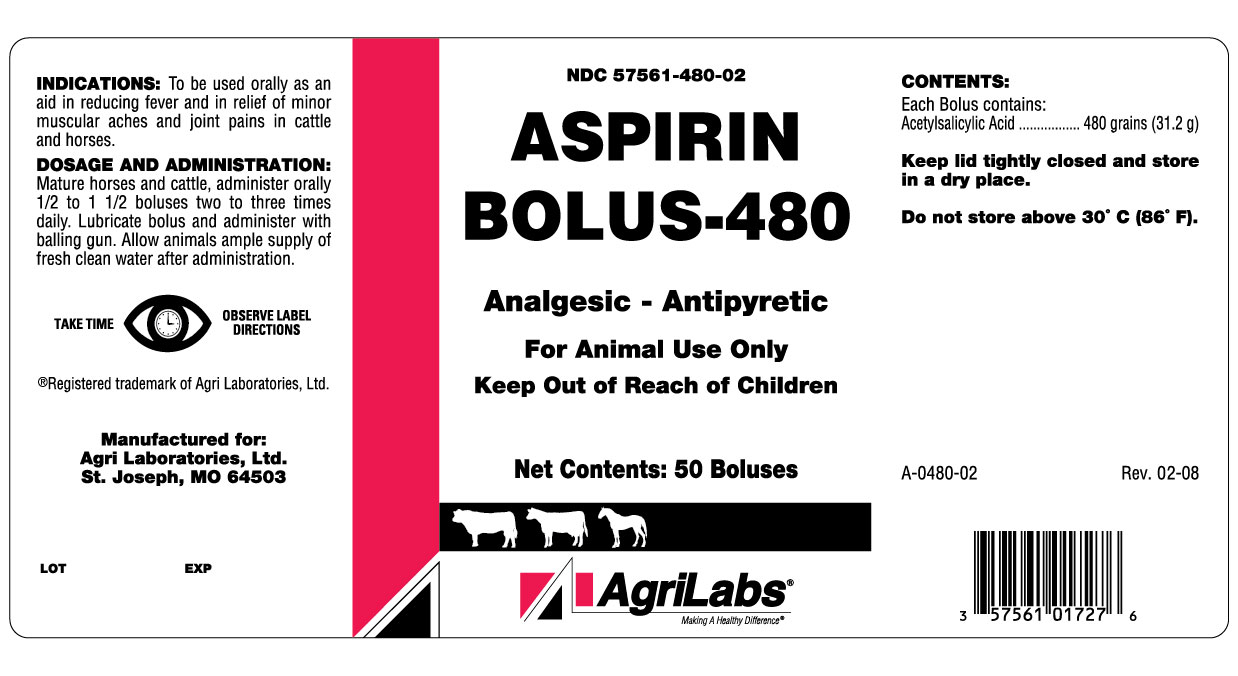 DRUG LABEL: ASPIRIN
NDC: 57561-480 | Form: TABLET
Manufacturer: Agri Laboratories, Ltd
Category: animal | Type: OTC ANIMAL DRUG LABEL
Date: 20140710

ACTIVE INGREDIENTS: ASPIRIN 31.2 g/1 1

ASPIRIN BOLUS-480

INDICATIONS AND USAGE

Analgesic - Antipyretic

For Animal Use Only

Keep Out of Reach of Children

INDICATIONS

To be used orally as an aid in reducing fever and in relief of minor muscular aches and joint pains in cattle and horses.

DOSAGE AND ADMINISTRATION

Mature Horses and Cattle, administer orally 1/2 to 1 1/2 boluses two to three times daily. Lubricate bolus and administer with balling gun. Allow animals ample supply of fresh clean water after administration.

CONTENTS

Each Bolus contains:

Acetylsalicylic Acid..........480 grains (31.2 g)

STORAGE AND HANDLING

Keep lid tightly closed and store in a dry place

Do not store above 30o C (86oF)

TAKE TIME OBSERVE LABEL DIRECTIONS